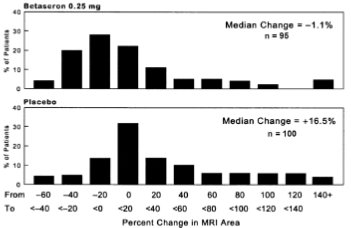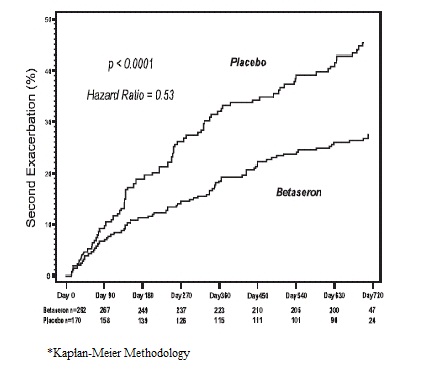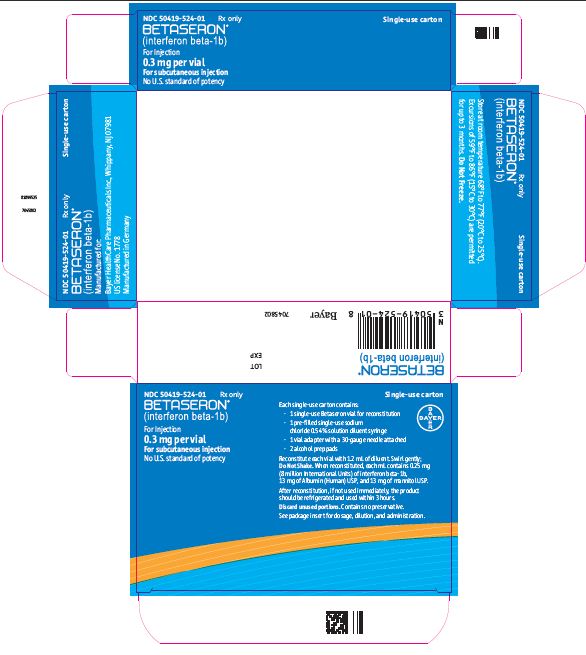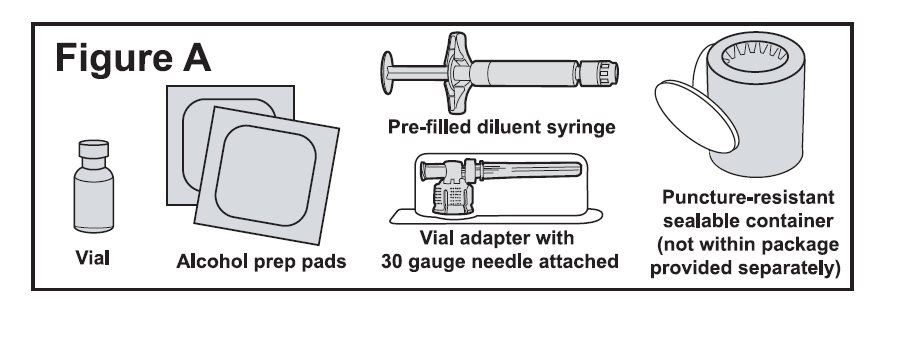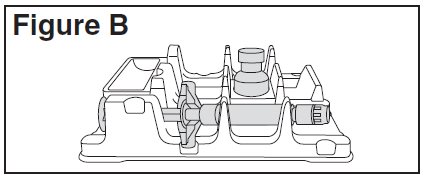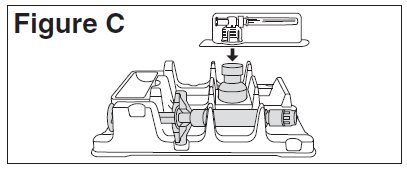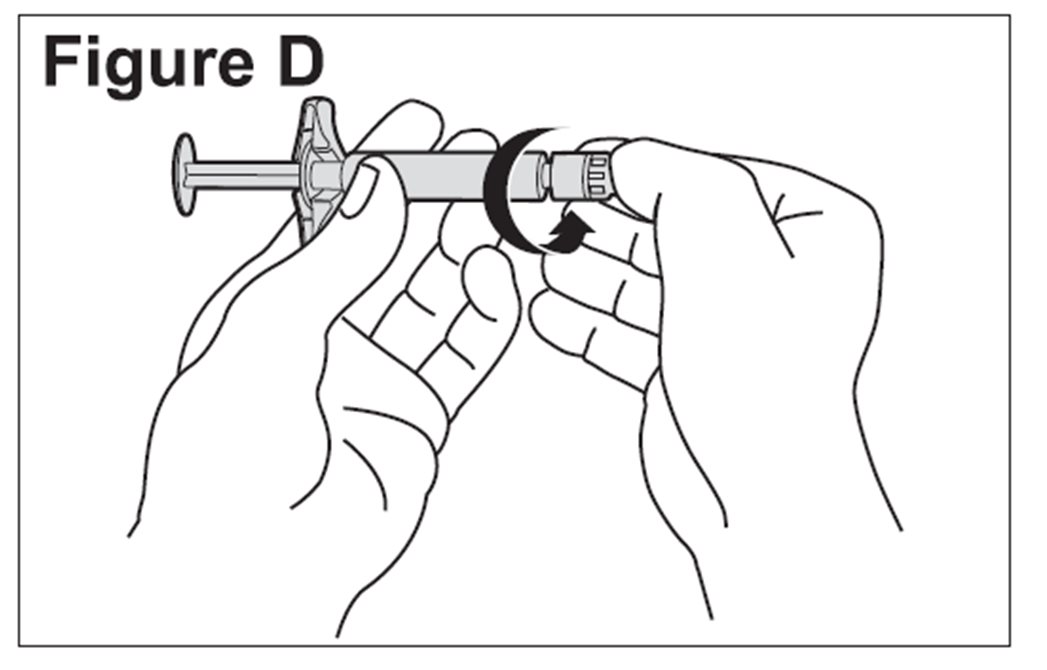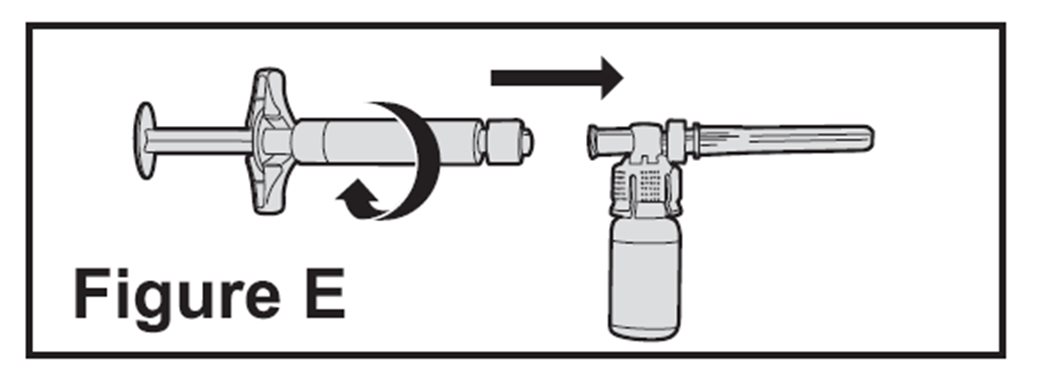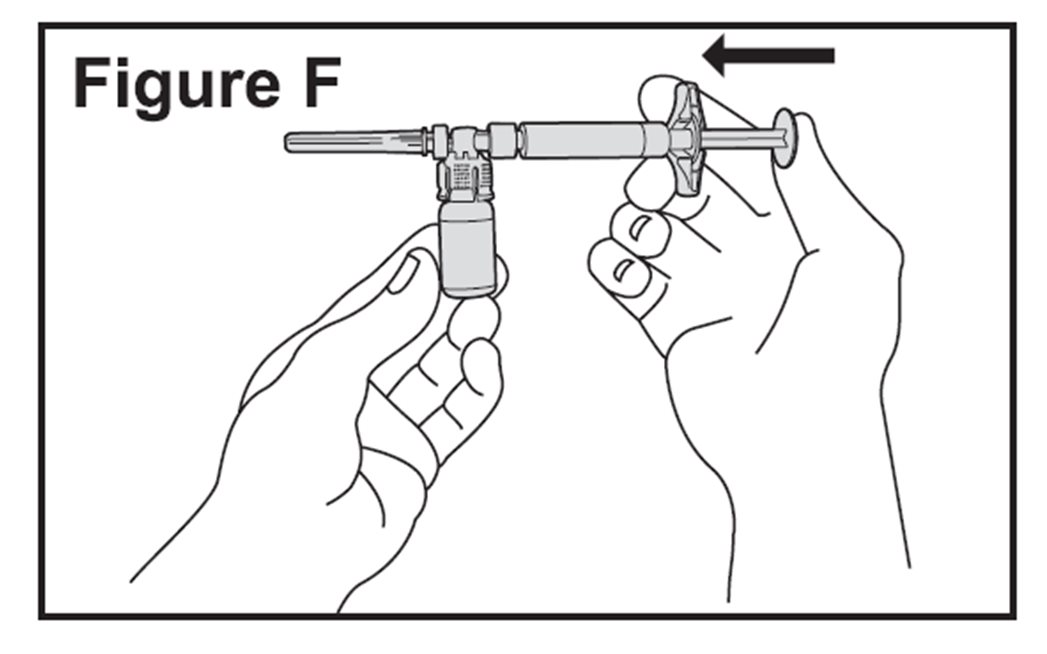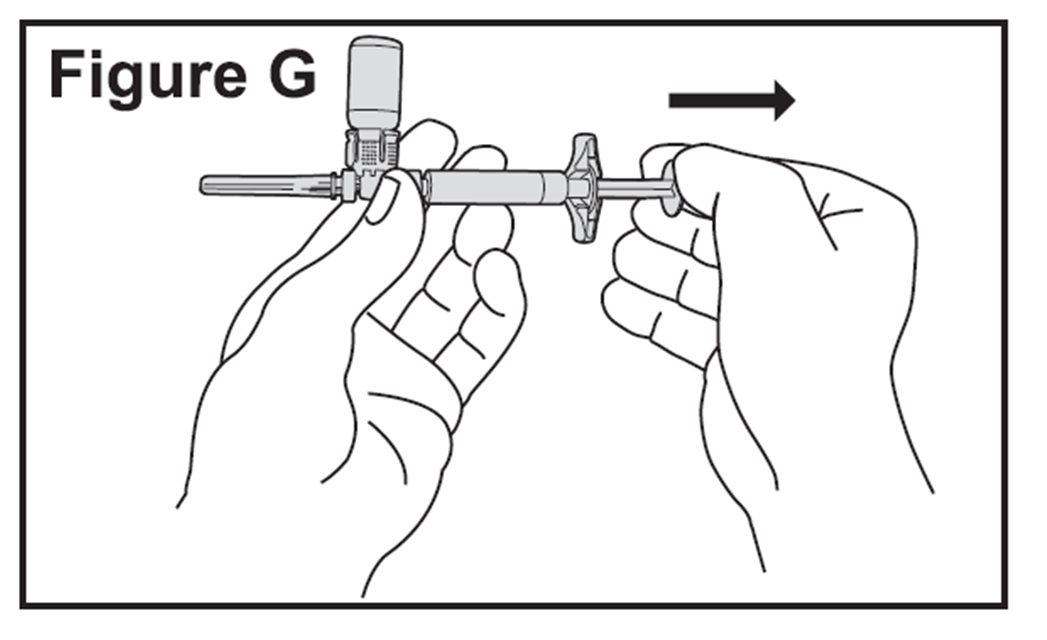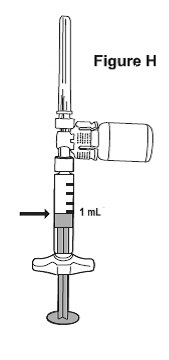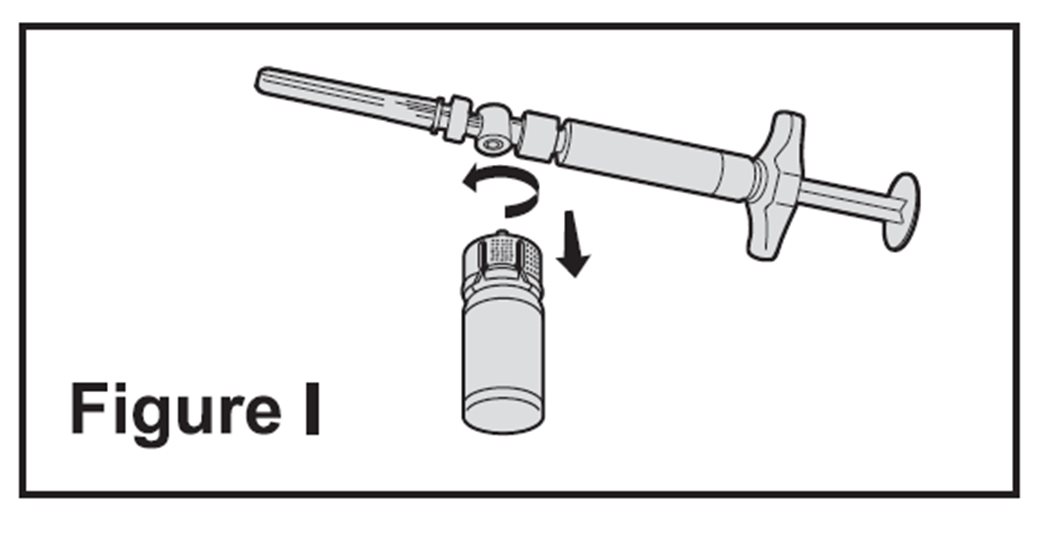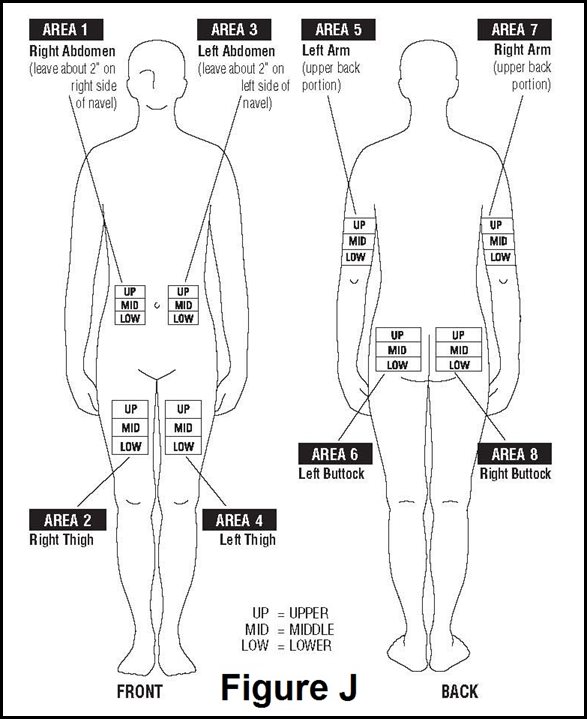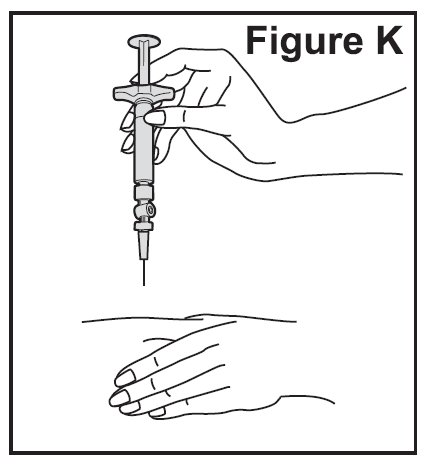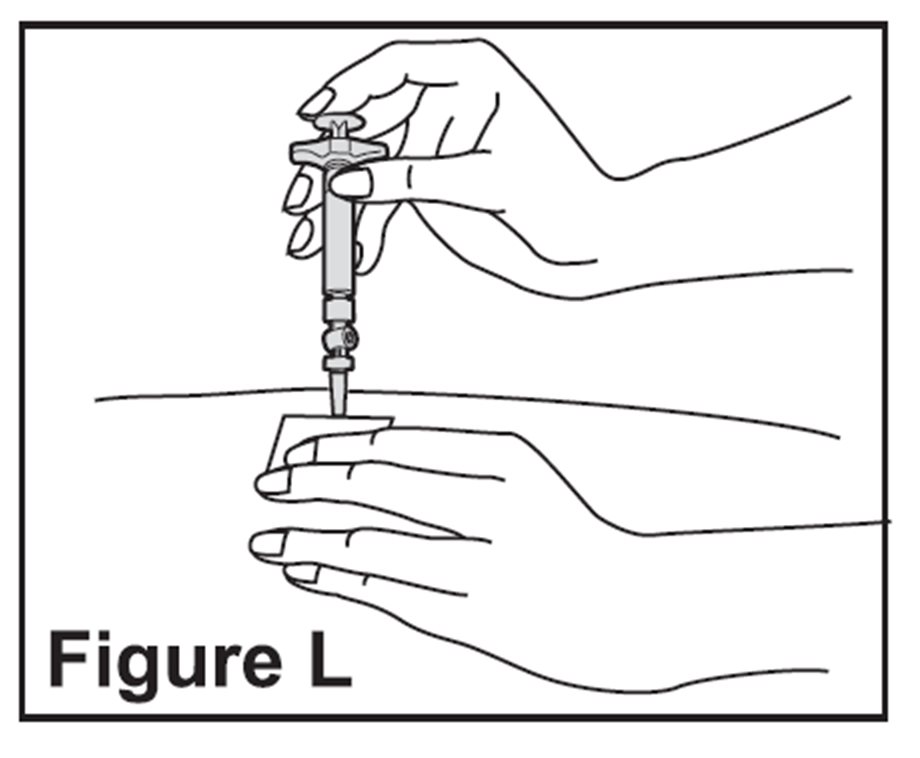 DRUG LABEL: Betaseron
NDC: 50419-524 | Form: KIT | Route: SUBCUTANEOUS
Manufacturer: Bayer HealthCare Pharmaceuticals Inc.
Category: prescription | Type: HUMAN PRESCRIPTION DRUG LABEL
Date: 20250930

ACTIVE INGREDIENTS: INTERFERON BETA-1B 0.25 mg/1 mL
INACTIVE INGREDIENTS: ALBUMIN HUMAN 15 mg/1 mL; MANNITOL 15 mg/1 mL; SODIUM CHLORIDE 5.4 mg/1 mL

HIGHLIGHTS OF PRESCRIBING INFORMATION

These highlights do not include all the information needed to use BETASERON safely and effectively. See full prescribing information for BETASERON.
BETASERON (interferon beta-1b) for injection, for subcutaneous use
Initial U.S. Approval: 1993

1 INDICATIONS AND USAGE

BETASERON is an interferon beta indicated for the treatment of relapsing forms of multiple sclerosis, to include clinically isolated syndrome, relapsing-remitting disease, and active secondary progressive disease, in adults. (1)

2 DOSAGE AND ADMINISTRATION

- For subcutaneous use only (2.1)
- The recommended dose is 0.25 mg every other day. Generally, start at 0.0625 mg (0.25 mL) every other day, and increase over a six-week period to 0.25 mg (1 mL) every other day. (2.1)
- Reconstitute lyophilized powder with supplied diluent (2.2)

3 DOSAGE FORMS AND STRENGTHS

For injection: 0.3 mg of lyophilized powder in a single-dose vial for reconstitution (3)

4 CONTRAINDICATIONS

History of hypersensitivity to natural or recombinant interferon beta, albumin or mannitol (4)

5 WARNINGS AND PRECAUTIONS

- Hepatic Injury: Monitor liver function tests and signs and symptoms of hepatic injury; consider discontinuing BETASERON if serious hepatic injury occurs. (5.1, 5.11)
- Anaphylaxis and Other Allergic Reactions: Discontinue if anaphylaxis occurs. (5.2)
- Depression and Suicide: Advise patients to immediately report any symptom of depression and/or suicidal ideation; consider discontinuation of BETASERON if depression occurs. (5.3)
- Congestive Heart Failure (CHF): Monitor patients with CHF for worsening of cardiac symptoms; consider discontinuation of BETASERON if worsening of CHF occurs. (5.4)
- Injection Site Reactions Including Necrosis: Do not administer BETASERON into affected area until fully healed; if multiple lesions occur, change injection site or discontinue BETASERON until healing of skin lesions. (5.5)
- Leukopenia: Monitor complete blood count. (5.6, 5.12)
- Thrombotic Microangiopathy: Cases of thrombotic microangiopathy (TMA) have been reported. Discontinue BETASERON if clinical symptoms and laboratory findings consistent with TMA occur and a relationship to BETASERON is suspected. (5.7)
- Pulmonary Arterial Hypertension: Cases of pulmonary arterial hypertension (PAH) have been reported in patients treated with interferon beta products, including BETASERON. Discontinue BETASERON if PAH is diagnosed. (5.8)
- Flu-like Symptom Complex: Consider analgesics and/or antipyretics on injection days. (5.9)
- Drug-induced Lupus Erythematosus: Cases of drug-induced lupus erythematosus have been reported. Discontinue BETASERON if patients develop new characteristic signs and symptoms. (5.11)

6 ADVERSE REACTIONS

In controlled clinical trials, the most common adverse reactions (at least 5% more frequent on BETASERON than on placebo) were: injection site reaction, lymphopenia, flu-like symptoms, myalgia, leukopenia, neutropenia, increased liver enzymes, headache, hypertonia, pain, rash, insomnia, abdominal pain, and asthenia. (6.1)

To report SUSPECTED ADVERSE REACTIONS, contact Bayer HealthCare Pharmaceuticals at 1-888-842-2937 or FDA at 1-800-FDA-1088 or www.fda.gov/medwatch.

8 USE IN SPECIFIC POPULATIONS

Pregnancy: Based on animal data, may cause fetal harm. (8.1)

FULL PRESCRIBING INFORMATION

1 INDICATIONS AND USAGE

BETASERON is indicated for the treatment of relapsing forms of multiple sclerosis (MS), to include clinically isolated syndrome, relapsing-remitting disease, and active secondary progressive disease, in adults.

2 DOSAGE AND ADMINISTRATION

2.1 Dosing Information

The recommended starting dose is 0.0625 mg (0.25 mL) subcutaneously every other day, with dose increases over a six-week period to the recommended dose of 0.25 mg (1 mL) every other day (see Table 1).

Table 1: Schedule for Dose Titration
 | BETASERON; Dose [Dosed every other day, subcutaneously] | Percentage of; recommended dose | Volume
Weeks 1-2 | 0.0625 mg | 25% | 0.25 mL
Weeks 3-4 | 0.125 mg | 50% | 0.5 mL
Weeks 5-6 | 0.1875 mg | 75% | 0.75 mL
Week 7 and thereafter | 0.25 mg | 100% | 1 mL

If a dose of BETASERON is missed, then it should be taken as soon as the patient remembers or is able to take it. The patient should not take BETASERON on two consecutive days. The next injection should be taken about 48 hours (two days) after that dose. If the patient accidentally takes more than their prescribed dose, or takes it on two consecutive days, they should be instructed to call their healthcare provider immediately.

2.2 Reconstitution of the Lyophilized Powder

(a) Prior to reconstitution, verify that the vial containing lyophilized BETASERON is not cracked or damaged. Do not use cracked or damaged vials.

(b) To reconstitute lyophilized BETASERON for injection, attach the pre-filled syringe containing the diluent (Sodium Chloride, 0.54% Solution) to the BETASERON vial using the vial adapter.

(c) Slowly inject 1.2 mL of diluent into the BETASERON vial.

(d) Gently swirl the vial to dissolve the lyophilized powder completely; do not shake. Foaming may occur during reconstitution or if the vial is swirled or shaken too vigorously. If foaming occurs, allow the vial to sit undisturbed until the foam settles.

(e) 1 mL of reconstituted BETASERON solution contains 0.25 mg of interferon beta-1b.

(f) After reconstitution, if not used immediately, refrigerate the reconstituted BETASERON solution at 35°F to 46°F (2°C to 8°C) and use within three hours. Do not freeze.

2.3 Important Administration Instructions

(a) BETASERON is intended for use under the guidance and supervision of a physician. If patients or caregivers are to administer BETASERON, train them in the proper technique for self‐administering subcutaneous injections using the prefilled syringe or the optional injection device. The BETACONNECT autoinjector has three adjustable injection depth settings; the healthcare provider should determine the proper depth setting and injection technique. Use only the syringes in the BETASERON packaging with the BETACONNECT autoinjector.

The initial BETASERON injection should be performed under the supervision of an appropriately qualified healthcare provider. Users should demonstrate competency in all aspects of the BETASERON injection prior to independent use. If a patient is to self‐administer BETASERON, the physical and cognitive ability of that patient to self‐administer and properly dispose of syringes should be assessed. Patients with severe neurological deficits should not self‐administer injections without assistance from a trained caregiver.

Appropriate instruction for self‐injection or injection by another person should be provided to the patient or their caregiver, including careful review of the BETASERON Medication Guide, the prefilled syringe Instructions for Use, and the BETACONNECT autoinjector Instructions for Use that accompanies the product.

(b) Visually inspect the reconstituted BETASERON solution before use; discard if it contains particulate matter or is discolored.

(c) Keeping the syringe and vial adapter in place, turn the assembly over so that the vial is on top. Withdraw the appropriate dose of BETASERON solution. Remove the vial from the vial adapter before injecting BETASERON.

(d) Use safe disposal procedures for needles and syringes.

(e) Do not re-use needles or syringes.

(f) Advise patients and caregivers to rotate sites for subcutaneous injections to minimize the likelihood of severe injection site reactions, including necrosis or localized infection [see Warnings and Precautions (5.5)].

2.4 Premedication for Flu-like Symptoms

Concurrent use of analgesics and/or antipyretics on treatment days may help ameliorate flu-like symptoms associated with BETASERON use [see Warnings and Precautions (5.8)].

3 DOSAGE FORMS AND STRENGTHS

For injection: 0.3 mg lyophilized powder in a single-dose vial for reconstitution.

4 CONTRAINDICATIONS

BETASERON is contraindicated in patients with a history of hypersensitivity to natural or recombinant interferon beta, Albumin (Human), or any other component of the formulation.

5 WARNINGS AND PRECAUTIONS

5.1 Hepatic Injury

Severe hepatic injury including cases of hepatic failure, some of which have been due to autoimmune hepatitis, has been rarely reported in patients taking BETASERON. In some cases, these events have occurred in the presence of other drugs or comorbid medical conditions that have been associated with hepatic injury. Consider the potential risk of BETASERON used in combination with known hepatotoxic drugs or other products (eg, alcohol) prior to BETASERON administration, or when adding new agents to the regimen of patients already on BETASERON. Monitor patients for signs and symptoms of hepatic injury. Consider discontinuing BETASERON if serum transaminase levels significantly increase, or if they are associated with clinical symptoms such as jaundice.

Asymptomatic elevation of serum transaminases is common in patients treated with BETASERON. In controlled clinical trials, elevations of SGPT to greater than five times baseline value were reported in 12% of patients receiving BETASERON (compared to 4% on placebo), and increases of SGOT to greater than five times baseline value were reported in 4% of patients receiving BETASERON (compared to 1% on placebo), leading to dose-reduction or discontinuation of treatment in some patients [see Adverse Reactions (6.1)]. Monitor liver function tests [see Warnings and Precautions (5.12)].

5.2 Anaphylaxis and Other Allergic Reactions

Anaphylaxis has been reported as a rare complication of BETASERON use. Other allergic reactions have included dyspnea, bronchospasm, tongue edema, skin rash and urticaria [see Adverse Reactions (6.1)]. Discontinue BETASERON if anaphylaxis occurs.

5.3 Depression and Suicide

Depression and suicide have been reported to occur with increased frequency in patients receiving interferon beta products, including BETASERON. Advise patients to report any symptom of depression and/or suicidal ideation to their healthcare provider. If a patient develops depression, discontinuation of BETASERON therapy should be considered.

In randomized controlled clinical trials, there were three suicides and eight suicide attempts among the 1532 patients on BETASERON compared to one suicide and four suicide attempts among 965 patients on placebo.

5.4 Congestive Heart Failure

Monitor patients with pre-existing congestive heart failure (CHF) for worsening of their cardiac condition during initiation of and continued treatment with BETASERON. While beta interferons do not have any known direct-acting cardiac toxicity, cases of CHF, cardiomyopathy, and cardiomyopathy with CHF have been reported in patients without known predisposition to these events, and without other known etiologies being established. In some cases, these events have been temporally related to the administration of BETASERON. Recurrence upon rechallenge was observed in some patients. Consider discontinuation of BETASERON if worsening of CHF occurs with no other etiology.

5.5 Injection Site Reactions Including Necrosis

Injection site reactions, including injection site necrosis, can occur with the use of interferon beta products, including BETASERON. Injection site necrosis (ISN) was reported in 4% of BETASERON-treated patients in controlled clinical trials (compared to 0% on placebo) [see Adverse Reactions (6.1)]. Typically, ISN occurs within the first four months of therapy, although postmarketing reports have been received of ISN occurring over one year after initiation of therapy. The necrotic lesions are typically 3 cm or less in diameter, but larger areas have been reported. Generally the necrosis has extended only to subcutaneous fat, but has extended to the fascia overlying muscle. In some lesions where biopsy results are available, vasculitis has been reported. For some lesions, debridement, and/or skin grafting have been required. In most cases healing was associated with scarring.

In controlled clinical trials, injection site reactions occurred in 78% of patients receiving BETASERON with injection site necrosis in 4%. Injection site inflammation (42%), injection site pain (16%), injection site hypersensitivity (4%), injection site necrosis (4%), injection site mass (2%), injection site edema (2%), and nonspecific reactions were significantly associated with BETASERON treatment. The incidence of injection site reactions tended to decrease over time. Approximately 69% of patients experienced injection site reactions during the first three months of treatment, compared to approximately 40% at the end of the studies.

Injection site abscesses and cellulitis have been reported in the postmarketing setting with use of interferon beta products including BETASERON. Some cases required treatment with hospitalization for surgical drainage and intravenous antibiotics. Periodically evaluate patient understanding and use of aseptic self-injection techniques and procedures, particularly if injection site necrosis has occurred. Patients should be advised of the importance of rotating injection sites with each dose. Whether to discontinue therapy following a single site of necrosis is dependent on the extent of necrosis. For patients who continue therapy with BETASERON after injection site necrosis has occurred, avoid administration of BETASERON into the affected area until it is fully healed. If multiple lesions occur, change injection site or discontinue therapy until healing occurs.

5.6 Leukopenia

In controlled clinical trials, leukopenia was reported in 18% of patients receiving BETASERON (compared to 6% on placebo), leading to a reduction of the dose of BETASERON in some patients [see Adverse Reactions (6.1)]. Monitoring of complete blood and differential white blood cell counts is recommended. Patients with myelosuppression may require more intensive monitoring of complete blood cell counts, with differential and platelet counts.

5.7 Thrombotic Microangiopathy

Cases of thrombotic microangiopathy (TMA), including thrombotic thrombocytopenic purpura and hemolytic uremic syndrome, some fatal, have been reported with interferon beta products, including BETASERON.

Cases have been reported several weeks to years after starting interferon beta products. If clinical symptoms and laboratory findings consistent with TMA occur and a relationship to BETASERON is suspected, discontinue treatment and manage as clinically indicated.

5.8 Pulmonary Arterial Hypertension

Cases of pulmonary arterial hypertension (PAH) have been reported with interferon beta products, including BETASERON. PAH has occurred in patients treated with interferon beta products in the absence of other contributory factors. Many of the reported cases required hospitalization, including one case with interferon beta in which the patient underwent a lung transplant. PAH has developed at various time points after initiating therapy with interferon beta products and may occur several years after starting treatment.

Patients who develop unexplained symptoms (e.g., dyspnea, new or increasing fatigue) should be assessed for PAH. If alternative etiologies have been ruled out and a diagnosis of PAH is confirmed, discontinue treatment and manage as clinically indicated.

5.9 Flu-like Symptom Complex

In controlled clinical trials, the rate of flu-like symptom complex for patients on BETASERON was 57% [see Adverse Reactions (6.1)]. The incidence decreased over time, with 10% of patients reporting flu-like symptom complex at the end of the studies. The median duration of flu-like symptom complex in Study 1 was 7.5 days [see Clinical Studies (14)]. Analgesics and/or antipyretics on treatment days may help ameliorate flu-like symptoms associated with BETASERON use.

5.10 Seizures

Seizures have been temporally associated with the use of beta interferons in clinical trials and postmarketing safety surveillance. It is not known whether these events were related to a primary seizure disorder, the effects of multiple sclerosis alone, the use of beta interferons, other potential precipitants of seizures (eg, fever), or to some combination of these.

5.11 Drug-induced Lupus Erythematosus

Cases of drug-induced lupus erythematosus have been reported with some interferon beta products, including BETASERON. Signs and symptoms of drug-induced lupus reported in BETASERON-treated patients have included rash, serositis, polyarthritis, nephritis, and Raynaud's phenomenon. Cases have occurred with positive serologic testing (including positive anti-nuclear and/or anti-double-stranded DNA antibody testing). If BETASERON-treated patients develop new signs and symptoms characteristic of this syndrome, BETASERON therapy should be stopped.

5.12 Monitoring for Laboratory Abnormalities

In addition to those laboratory tests normally required for monitoring patients with multiple sclerosis, complete blood and differential white blood cell counts, platelet counts and blood chemistries, including liver function tests, are recommended at regular intervals (one, three, and six months) following introduction of BETASERON therapy, and then periodically thereafter in the absence of clinical symptoms.

6 ADVERSE REACTIONS

The following serious adverse reactions are discussed in more details in other sections of labeling:

- Hepatic Injury [see Warnings and Precautions (5.1)]
- Anaphylaxis and Other Allergic Reactions [see Warnings and Precautions (5.2)]
- Depression and Suicide [see Warnings and Precautions (5.3)]
- Congestive Heart Failure [see Warnings and Precautions (5.4)]
- Injection Site Reactions Including Necrosis [see Warnings and Precautions (5.5)]
- Leukopenia [see Warnings and Precautions (5.6)]
- Thrombotic Microangiopathy [see Warnings and Precautions (5.7)]
- Pulmonary Arterial Hypertension [see Warnings and Precautions (5.8)]
- Flu-like Symptom Complex [see Warnings and Precautions (5.9)]
- Seizures [see Warnings and Precautions (5.10)]
- Drug Induced Lupus Erythematosus [see Warnings and Precautions (5.11)]

6.1 Clinical Trials Experience

Because clinical trials are conducted under widely varying conditions and over varying lengths of time, adverse reaction rates observed in the clinical trials of BETASERON cannot be directly compared to rates in clinical trials of other drugs, and may not reflect the rates observed in practice.

Among 1407 patients with MS treated with BETASERON 0.25 mg every other day (including 1261 patients treated for greater than one year), the most commonly reported adverse reactions (at least 5% more frequent on BETASERON than on placebo) were injection site reaction, lymphopenia, flu-like symptoms, myalgia leukopenia, neutropenia, increased liver enzymes, headache, hypertonia, pain, rash, insomnia, abdominal pain, and asthenia. The most frequently reported adverse reactions resulting in clinical intervention (for example, discontinuation of BETASERON, adjustment in dosage, or the need for concomitant medication to treat an adverse reaction symptom) were depression, flu-like symptom complex, injection site reactions, leukopenia, increased liver enzymes, asthenia, hypertonia, and myasthenia.

Table 2 enumerates adverse reactions and laboratory abnormalities that occurred among patients treated with 0.25 mg of BETASERON every other day by subcutaneous injection in the pooled placebo-controlled trials (Study 1-4) at an incidence that was at least 2% more than that observed in the placebo-treated patients [see Clinical Studies (14)].

Table 2: Adverse Reactions and Laboratory Abnormalities in Patients with MS in Pooled Studies 1, 2, 3, and 4
Adverse Reaction | Placebo (N=965) | BETASERON (N=1407)
Blood and lymphatic system disorders
Lymphocytes count decreased (<1500/mm3) | 66% | 86%
Absolute neutrophil count decreased (<1500/mm3) | 5% | 13%
White blood cell count decreased (<3000/mm3) | 4% | 13%
Lymphadenopathy | 3% | 6%
Nervous system disorders
Headache | 43% | 50%
Insomnia | 16% | 21%
Incoordination | 15% | 17%
Vascular disorders
Hypertension | 4% | 6%
Respiratory, thoracic and mediastinal disorders
Dyspnea | 3% | 6%
Gastrointestinal disorders
Abdominal pain | 11% | 16%
Hepatobiliary disorders
Alanine aminotransferase increased (SGPT > 5 times baseline) | 4% | 12%
Aspartate aminotransferase increased (SGOT > 5 times baseline) | 1% | 4%
Skin and subcutaneous tissue disorders
Rash | 15% | 21%
Skin disorder | 8% | 10%
Musculoskeletal and; connective tissue disorders
Hypertonia | 33% | 40%
Myalgia | 14% | 23%
Renal and urinary disorders
Urinary urgency | 8% | 11%
Reproductive system and breast disorders
Metrorrhagia | 7% | 9%
Impotence | 6% | 8%
General disorders and administration site conditions
Injection site reaction ["Injection site reaction" comprises all adverse reactions occurring at the injection site (except injection site necrosis), that is, the following terms: injection site reaction, injection site hemorrhage, injection site hypersensitivity, injection site inflammation, injection site mass, injection site pain, injection site edema and injection site atrophy.] | 26% | 78%
Asthenia | 48% | 53%
Flu-like symptoms (complex) ["Flu-like symptom (complex)" denotes flu syndrome and/or a combination of at least two adverse reactions from fever, chills, myalgia, malaise, sweating.] | 37% | 57%
Pain | 35% | 42%
Fever | 19% | 31%
Chills | 9% | 21%
Peripheral edema | 10% | 12%
Chest pain | 6% | 9%
Malaise | 3% | 6%
Injection site necrosis | 0% | 4%

In addition to the Adverse Reactions listed in Table 2, the following adverse reactions occurred more frequently on BETASERON than on placebo, but with a difference smaller than 2%: alopecia, anxiety, arthralgia, constipation, diarrhea, dizziness, dyspepsia, dysmenorrhea, leg cramps, menorrhagia, myasthenia, nausea, nervousness, palpitations, peripheral vascular disorder, prostatic disorder, tachycardia, urinary frequency, vasodilatation, and weight increase.

Laboratory Abnormalities

In the four clinical trials (Studies 1, 2, 3, and 4), leukopenia was reported in 18% and 6% of patients in BETASERON- and placebo-treated groups, respectively. No patients were withdrawn or dose reduced for neutropenia in Study 1. Three percent (3%) of patients in Studies 2 and 3 experienced leukopenia and were dose-reduced. Other abnormalities included increase of SGPT to greater than five times baseline value (12%), and increase of SGOT to greater than five times baseline value (4%). In Study 1, two patients were dose reduced for increased hepatic enzymes; one continued on treatment and one was ultimately withdrawn. In Studies 2 and 3, 1.5% of BETASERON patients were dose-reduced or interrupted treatment for increased hepatic enzymes. In Study 4, 1.7% of patients were withdrawn from treatment due to increased hepatic enzymes, two of them after a dose reduction. In Studies 1-4, nine (0.6%) patients were withdrawn from treatment with BETASERON for any laboratory abnormality, including four (0.3%) patients following dose reduction.

6.2 Immunogenicity

As with all therapeutic proteins, there is a potential for immunogenicity. Serum samples were monitored for the development of antibodies to BETASERON during Study 1. In patients receiving 0.25 mg every other day 56/124 (45%) were found to have serum neutralizing activity at one or more of the time points tested. In Study 4, neutralizing activity was measured every 6 months and at end of study. At individual visits after start of therapy, activity was observed in 17% up to 25% of the BETASERON-treated patients. Such neutralizing activity was measured at least once in 75 (30%) out of 251 BETASERON patients who provided samples during treatment phase; of these, 17 (23%) converted to negative status later in the study. Based on all the available evidence, the relationship between antibody formation and clinical safety or efficacy is not known.

These data reflect the percentage of patients whose test results were considered positive for antibodies to BETASERON using a biological neutralization assay that measures the ability of immune sera to inhibit the production of the interferon-inducible protein, MxA. Neutralization assays are highly dependent on the sensitivity and specificity of the assay. Additionally, the observed incidence of neutralizing activity in an assay may be influenced by several factors including sample handling, timing of sample collection, concomitant medications, and underlying disease. For these reasons, comparison of the incidence of antibodies to BETASERON with the incidence of antibodies to other products may be misleading.

Anaphylactic reactions have been reported with the use of BETASERON [see Warnings and Precautions (5.2)].

6.3 Postmarketing Experience

The following adverse reactions have been identified during postapproval use of BETASERON. Because these reactions are reported voluntarily from a population of uncertain size, it is not always possible to reliably estimate their frequency or establish a causal relationship to drug exposure.

Blood and lymphatic system disorders: Anemia, Thrombocytopenia, Hemolytic anemia

Endocrine disorders: Hypothyroidism, Hyperthyroidism, Thyroid dysfunction

Metabolism and nutrition disorders: Triglyceride increased, Anorexia, Weight decrease, Weight increase

Psychiatric disorders: Anxiety, Confusion, Emotional lability

Nervous system disorders: Convulsion, Dizziness, Psychotic symptoms

Cardiac disorders: Cardiomyopathy, Palpitations, Tachycardia

Vascular disorders: Vasodilatation

Respiratory, thoracic and mediastinal disorders: Bronchospasm, Pulmonary Arterial Hypertension

Gastrointestinal disorders: Diarrhea, Nausea, Pancreatitis, Vomiting

Hepatobiliary disorders: Hepatitis, Gamma GT increased

Skin and subcutaneous tissue disorders: Alopecia, Pruritus, Skin discoloration, Urticaria

Musculoskeletal and connective tissue disorders: Arthralgia

Reproductive system and breast disorder: Menorrhagia

General disorders and administration site conditions: Fatal capillary leak syndrome^1

^1The administration of cytokines to patients with a pre-existing monoclonal gammopathy has been associated with the development of this syndrome.

8 USE IN SPECIFIC POPULATIONS

8.1 Pregnancy

Risk Summary

Although there have been no well-controlled studies in pregnant women, available data, which includes prospective observational studies, have not generally indicated a drug-associated risk of major birth defects with interferon beta-1b during pregnancy. Administration of BETASERON to monkeys during gestation resulted in increased embryo-fetal death at or above exposures greater than 3 times the human therapeutic dose (see Animal Data).

In the U.S. general population, the estimated background risk of major birth defects and miscarriage in clinically recognized pregnancies is 2-4% and 15-20%, respectively. The background risk of major birth defects and miscarriage for the indicated population is unknown.

Data

Human Data

The majority of the observational studies reporting on pregnancies exposed to interferon beta-1b did not identify an association between the use of interferon beta-1b during pregnancy and an increased risk of major birth defects

Animal Data

When BETASERON (doses ranging from 0.028 to 0.42 mg/kg/day) was administered to pregnant rhesus monkeys throughout the period of organogenesis (gestation days 20 to 70), a dose-related abortifacient effect was observed. The low-effect dose is approximately 3 times the recommended human dose of 0.25 mg on a body surface area (mg/m^2) basis. A no-effect dose for embryo-fetal developmental toxicity in rhesus monkeys was not established.

8.2 Lactation

Risk Summary

There are no data on the presence of BETASERON in human milk, the effects on the breastfed infant, or the effects of the drug on milk production.

The developmental and health benefits of breastfeeding should be considered along with the mother's clinical need for BETASERON and any potential adverse effects on the breastfed child from BETASERON or from the underlying maternal condition.

8.4 Pediatric Use

Safety and efficacy in pediatric patients have not been established.

8.5 Geriatric Use

Clinical studies of BETASERON did not include sufficient numbers of patients aged 65 and over to determine whether they respond differently than younger patients.

11 DESCRIPTION

Interferon beta-1b is a purified, sterile, lyophilized protein product produced by recombinant DNA techniques. Interferon beta-1b is manufactured by bacterial fermentation of a strain of Escherichia coli that bears a genetically engineered plasmid containing the gene for human interferon betaser17. The native gene was obtained from human fibroblasts and altered in a way that substitutes serine for the cysteine residue found at position 17. Interferon beta-1b has 165 amino acids and an approximate molecular weight of 18,500 daltons. It does not include the carbohydrate side chains found in the natural material.

The specific activity of BETASERON is approximately 32 million international units (IU)/mg interferon beta-1b. Each vial contains 0.3 mg of interferon beta-1b. The unit measurement is derived by comparing the antiviral activity of the product to the World Health Organization (WHO) reference standard of recombinant human interferon beta. Mannitol, USP and Albumin (Human), USP (15 mg each/vial) are added as stabilizers.

Lyophilized BETASERON is a sterile, white to off-white powder, for subcutaneous injection after reconstitution with the diluent supplied (Sodium Chloride, 0.54% Solution). Albumin (Human) USP and Mannitol, USP (15 mg each/vial) are added as stabilizers.

12 CLINICAL PHARMACOLOGY

12.1 Mechanism of Action

The mechanism of action of BETASERON (interferon beta-1b) in patients with multiple sclerosis is unknown.

12.2 Pharmacodynamics

Interferons (IFNs) are a family of naturally occurring proteins, produced by eukaryotic cells in response to viral infection and other biologic agents. Three major types of interferons have been defined: type 1 (IFN-alpha, beta, epsilon, kappa and omega), type II (IFN–gamma) and type III (IFN-lambda). Interferon-beta is a member of the type I subset of interferons. The type I interferons have considerably overlapping but also distinct biologic activities. The bioactivities of all IFNs, including IFN-beta, are induced via their binding to specific receptors on the membranes of human cells. Differences in the bioactivities induced by the three major subtypes of IFNs likely reflect differences in the signal transduction pathways induced by signaling through their cognate receptors.

Interferon beta-1b receptor binding induces the expression of proteins that are responsible for the pleiotropic bioactivities of interferon beta-1b. A number of these proteins (including neopterin, β2-microglobulin, MxA protein, and IL-10) have been measured in blood fractions from BETASERON-treated patients and BETASERON-treated healthy volunteers. Immunomodulatory effects of interferon beta-1b include the enhancement of suppressor T cell activity, reduction of pro-inflammatory cytokine production, down-regulation of antigen presentation, and inhibition of lymphocyte trafficking into the central nervous system. It is not known if these effects play an important role in the observed clinical activity of BETASERON in multiple sclerosis (MS).

12.3 Pharmacokinetics

Because serum concentrations of interferon beta-1b are low or not detectable following subcutaneous administration of 0.25 mg or less of BETASERON, pharmacokinetic information in patients with MS receiving the recommended dose of BETASERON is not available.

Following single and multiple daily subcutaneous administrations of 0.5 mg BETASERON to healthy volunteers (N=12), serum interferon beta-1b concentrations were generally below 100 IU/mL. Peak serum interferon beta-1b concentrations occurred between one to eight hours, with a mean peak serum interferon concentration of 40 IU/mL. Bioavailability, based on a total dose of 0.5 mg BETASERON given as two subcutaneous injections at different sites, was approximately 50%.

After intravenous administration of BETASERON (0.006 mg to 2 mg), similar pharmacokinetic profiles were obtained from healthy volunteers (N=12) and from patients with diseases other than MS (N=142). In patients receiving single intravenous doses up to 2 mg, increases in serum concentrations were dose proportional. Mean serum clearance values ranged from 9.4 mL/min•kg-1 to 28.9 mL/min•kg-1 and were independent of dose. Mean terminal elimination half-life values ranged from 8 minutes to 4.3 hours and mean steady-state volume of distribution values ranged from 0.25 L/kg to 2.88 L/kg. Three-times-a-week intravenous dosing for two weeks resulted in no accumulation of interferon beta-1b in sera of patients. Pharmacokinetic parameters after single and multiple intravenous doses of BETASERON were comparable.

Following every other day subcutaneous administration of 0.25 mg BETASERON in healthy volunteers, biologic response marker levels (neopterin, β2- microglobulin, MxA protein, and the immunosuppressive cytokine, IL-10) increased significantly above baseline six-twelve hours after the first BETASERON dose. Biologic response marker levels peaked between 40 and 124 hours and remained elevated above baseline throughout the seven-day (168-hour) study. The relationship between serum interferon beta-1b levels or induced biologic response marker levels and the clinical effects of interferon beta-1b in multiple sclerosis is unknown.

Drug Interaction Studies

No formal drug interaction studies have been conducted with BETASERON.

13 NONCLINICAL TOXICOLOGY

13.1 Carcinogenesis, Mutagenesis, Impairment of Fertility

Carcinogenesis

BETASERON has not been tested for its carcinogenic potential in animals.

Mutagenesis

BETASERON was not genotoxic in the in vitro Ames bacterial test or the in vitro chromosomal aberration assay in human peripheral blood lymphocytes. BETASERON treatment of mouse BALBc-3T3 cells did not result in increased transformation frequency in an in vitro model of tumor transformation.

Impairment of Fertility

Administration of BETASERON (doses of up to 0.33 mg/kg/day) to normally cycling female rhesus monkeys had no apparent adverse effects on either menstrual cycle duration or associated hormonal profiles (progesterone and estradiol) when administered over three consecutive menstrual cycles. The highest dose tested is approximately 30 times the recommended human dose of 0.25 mg on a body surface area (mg/m2) basis. The potential for other effects on fertility or reproductive performance was not evaluated.

14 CLINICAL STUDIES

The clinical effects of BETASERON were studied in four randomized, multicenter, double-blind, placebo-controlled studies in patients with multiple sclerosis (Studies 1, 2, 3, and 4).

Patients with Relapsing-Remitting Multiple Sclerosis

The effectiveness of BETASERON in relapsing-remitting MS (RRMS) was evaluated in a double-blind, multiclinic, randomized, parallel, placebo controlled clinical study of two years duration (Study 1). The study enrolled MS patients, aged 18 to 50, who were ambulatory [Kurtzke Expanded Disability Status Scale (EDSS) of ≤ 5.5 – score 5.5 is ambulatory for 100 meters, disability precludes full daily activities], exhibited a relapsing-remitting clinical course, met Poser's criteria for clinically definite and/or laboratory supported definite MS and had experienced at least two exacerbations over two years preceding the trial without exacerbation in the preceding month. The EDSS score is a method of quantifying disability in patients with MS and ranges from 0 (normal neurologic exam) to 10 (death due to MS). Patients who had received prior immunosuppressant therapy were excluded.

An exacerbation was defined as the appearance of a new clinical sign/symptom or the clinical worsening of a previous sign/symptom (one that had been stable for at least 30 days) that persisted for a minimum of 24 hours.

Patients selected for study were randomized to treatment with either placebo (N=123), 0.05 mg of BETASERON (N=125), or 0.25 mg of BETASERON (N=124) self-administered subcutaneously every other day. Outcome based on the 372 randomized patients was evaluated after two years.

Patients who required more than three 28-day courses of corticosteroids were removed from the study. Minor analgesics (acetaminophen, codeine), antidepressants, and oral baclofen were allowed ad libitum, but chronic nonsteroidal anti-inflammatory drug (NSAID) use was not allowed.

The primary protocol-defined outcome measures were 1) frequency of exacerbations per patient and 2) proportion of exacerbation free patients. A number of secondary clinical and magnetic resonance imaging (MRI) measures were also employed. All patients underwent annual T2 MRI imaging and a subset of 52 patients at one site had MRIs performed every six weeks for assessment of new or expanding lesions.

The study results are shown in Table 3.

Table 3: Two-Year RRMS Study Results of Primary and Secondary Clinical Outcomes (Study 1)
Efficacy Parameters |  | Treatment Groups |  |  | Statistical Comparisons p-value
Primary End Points |  | Placebo (N=123) | BETASERON 0.05 mg (N=125) | BETASERON 0.25 mg (N=124) | Placebo vs 0.05 mg | 0.05 mg vs 0.25 mg | Placebo vs 0.25 mg
Annual exacerbation rate |  | 1.31 | 1.14 | 0.9 | 0.005 | 0.113 | 0.0001
Proportion of exacerbation-free patients [14 exacerbation free patients (0 from placebo, six from 0.05 mg, and eight from 0.25 mg) dropped out of the study before completing six months of therapy. These patients are excluded from this analysis.] |  | 16% | 18% | 25% | 0.609 | 0.288 | 0.094
Exacerbation frequency per patient | 0; 1; 2; 3; 4; > 5 | 20%; 32%; 20%; 15%; 15%; 21% | 22%; 31%; 28%; 15%; 7%; 16% | 29%; 39%; 17%; 14%; 9%; 8% | 0.151 | 0.077 | 0.001
Secondary Endpoints [Sequelae and Functional Neurologic Status, both required by protocol, were not analyzed individually but are included as a function of the EDSS.]
Median number of months to first on-study exacerbation |  | 5 | 6 | 9 | 0.299 | 0.097 | 0.01
Rate of moderate or severe exacerbations per year |  | 0.47 | 0.29 | 0.23 | 0.02 | 0.257 | 0.001
Mean number of moderate or severe exacerbation days per patient |  | 44 | 33 | 20 | 0.229 | 0.064 | 0.001
Mean change in EDSS score [EDSS scores range from 1-10, with higher scores reflecting greater disability.] at endpoint |  | 0.21 | 0.21 | -0.07 | 0.995 | 0.108 | 0.144
Mean change in Scripps score [Scripps neurologic rating scores range from 0-100, with smaller scores reflecting greater disability.] at endpoint |  | -0.53 | -0.5 | 0.66 | 0.641 | 0.051 | 0.126
Median duration in days per exacerbation |  | 36 | 33 | 36 | ND [ND = Not done.] | ND | ND
% change in mean MRI lesion area at endpoint |  | 21.4% | 9.8% | -0.9% | 0.015 | 0.019 | 0.0001

Of the 372 RRMS patients randomized, 72 (19%) failed to complete two full years on their assigned treatments.

Over the two-year period in Study 1, there were 25 MS-related hospitalizations in the 0.25 mg BETASERON-treated group compared to 48 hospitalizations in the placebo group. In comparison, non-MS hospitalizations were evenly distributed among the groups, with 16 in the 0.25 mg BETASERON group and 15 in the placebo group. The average number of days of MS-related steroid use was 41 days in the 0.25 mg BETASERON group and 55 days in the placebo group (p=0.004).

MRI data were also analyzed for patients in this study. A frequency distribution of the observed percent changes in MRI area at the end of two years was obtained by grouping the percentages in successive intervals of equal width. Figure 1 displays a histogram of the proportions of patients, which fell into each of these intervals. The median percent change in MRI area for the 0.25 mg group was -1.1%, which was significantly smaller than the 16.5% observed for the placebo group (p=0.0001).

Figure 1: Distribution of Change in MRI Area in Patients with RRMS in Study 1

In an evaluation of frequent MRI scans (every six weeks) on 52 patients at one site in Study 1, the percent of scans with new or expanding lesions was 29% in the placebo group and 6% in the 0.25 mg treatment group (p=0.006).

Patients with Secondary Progressive Multiple Sclerosis

Studies 2 and 3 were multicenter, randomized, double-blind, placebo controlled trials conducted to assess the effect of BETASERON in patients with secondary progressive MS (SPMS). Study 2 was conducted in Europe and Study 3 was conducted in North America. Both studies enrolled patients with clinically definite or laboratory-supported MS in the secondary progressive phase, and who had evidence of disability progression (both Study 2 and 3) or two relapses (Study 2 only) within the previous two years. Baseline Kurtzke expanded disability status scale (EDSS) scores ranged from 3.0 to 6.5. Patients in Study 2 were randomized to receive BETASERON 0.25 mg (N=360) or placebo (N=358). Patients in Study 3 were randomized to BETASERON 0.25 mg (N=317), BETASERON 0.16 mg/m2 of body surface area (N=314, mean assigned dose 0.3 mg), or placebo (N=308). Test agents were administered subcutaneously, every other day for three years.

The primary outcome measure was progression of disability, defined as a 1.0 point increase in the EDSS score, or a 0.5 point increase for patients with baseline EDSS ≥ 6.0. In Study 2, time to progression in EDSS was longer in the BETASERON treatment group (p=0.005), with estimated annualized rates of progression of 16% and 19% in the BETASERON and placebo groups, respectively. In Study 3, the rates of progression did not differ significantly between treatment groups, with estimated annualized rates of progression of 12%, 14%, and 12% in the BETASERON fixed dose, surface area-adjusted dose, and placebo groups, respectively.

Multiple analyses, including covariate and subset analyses based on sex, age, disease duration, clinical disease activity prior to study enrollment, MRI measures at baseline and early changes in MRI following treatment were evaluated in order to interpret the discordant study results. No demographic or disease-related factors enabled identification of a patient subset where BETASERON treatment was predictably associated with delayed progression of disability.

In Studies 2 and 3, like Study 1, a statistically significant decrease in the incidence of relapses associated with BETASERON treatment was demonstrated. In Study 2, the mean annual relapse rates were 0.42 and 0.63 in the BETASERON and placebo groups, respectively (p<0.001). In Study 3, the mean annual relapse rates were 0.16, 0.20, and 0.28, for the fixed dose, surface area-adjusted dose, and placebo groups, respectively (p<0.02).

MRI endpoints in both Study 2 and Study 3 showed smaller increases in T2 MRI lesion area and decreased number of active MRI lesions in patients in the BETASERON groups compared to the placebo group.

Patients with an Isolated Demyelinating Event and Typical MS Lesions on Brain MRI

In Study 4, 468 patients who had recently (within 60 days) experienced an isolated demyelinating event, and who had lesions typical of multiple sclerosis on brain MRI were randomized to receive either 0.25 mg BETASERON (N = 292) or placebo (N=176) subcutaneously every other day (ratio 5:3). The primary outcome measure was time to development of a second exacerbation with involvement of at least two distinct anatomical regions. Secondary outcomes were brain MRI measures, including the cumulative number of newly active lesions, and the absolute change in T2 lesion volume. Patients were followed for up to two years or until they fulfilled the primary endpoint.

Eight percent of subjects on BETASERON and 6% of subjects on placebo withdrew from the study for a reason other than the development of a second exacerbation. Time to development of a second exacerbation was significantly delayed in patients treated with BETASERON compared to patients treated with placebo (p<0.0001). The Kaplan-Meier estimates of the percentage of patients developing an exacerbation within 24 months were 45% in the placebo group and 28% of the BETASERON group (Figure 2). The risk for developing a second exacerbation in the BETASERON group was 53% of the risk in the placebo group (Hazard ratio= 0.53; 95% confidence interval 0.39 to 0.73).

Figure 2: Onset of Second Exacerbation by Time in Patients with Isolated Demyelinating Event with Typical MS Lesions on Brain MRI in Study 4*

In Study 4, patients treated with BETASERON demonstrated a lower number of newly active lesions during the course of the study. A significant difference between BETASERON and placebo was not seen in the absolute change in T2 lesion volume during the course of the study.

16 HOW SUPPLIED/STORAGE AND HANDLING

16.1 How Supplied

BETASERON is supplied as a lyophilized powder in a clear glass, single-dose vial (3 mL capacity). Each carton contains 5 single-dose cartons (NDC 50419-524-05) or 14 single-dose cartons (NDC 50419-524-35).

Each single-dose carton contains:

A single-dose vial containing 0.3 mg BETASERON (interferon beta-1b)

A pre-filled single-dose syringe containing 1.2 mL diluent (Sodium Chloride, 0.54% solution)

A vial adapter with a 30-gauge needle attached

2 alcohol prep pads

The optional BETACONNECT autoinjector is not supplied with BETASERON, but is available for patients with a prescription for BETASERON by calling the BETAPLUS patient support program toll-free number at 1-800-788-1467.

16.2 Stability and Storage

BETASERON and the diluent are for single-dose only. Discard unused portions. The reconstituted product contains no preservative. Store BETASERON vials between 36°F to 86°F (2°C to 30°C). After reconstitution, if not used immediately, refrigerate the reconstituted solution and use within three hours. Do not freeze.

17 PATIENT COUNSELING INFORMATION

See FDA-approved patient labeling (Medication Guide and Instructions for Use).

Instruct patients to carefully read the supplied BETASERON Medication Guide and caution patients not to change the BETASERON dose or schedule of administration without medical consultation.

Instruction on Self-Injection Technique and Procedures

Provide appropriate instruction for reconstitution of BETASERON and methods of self-injection, including careful review of the BETASERON Medication Guide. Instruct patients in the use of aseptic technique when administering BETASERON.

Tell patients not to re-use needles or syringes and instruct patients on safe disposal procedures. Advise patients of the importance of rotating areas of injection with each dose, to minimize the likelihood of severe injection site reactions, including necrosis or localized infection [see Medication Guide].

Hepatic Injury

Advise patients that severe hepatic injury, including hepatic failure, has been reported during the use of BETASERON.

Inform patients of symptoms of hepatic dysfunction, and instruct patients to report them immediately to their healthcare provider [see Warnings and Precautions (5.1)].

Anaphylaxis and Other Allergic Reactions

Advise patients of the symptoms of allergic reactions and anaphylaxis, and instruct patients to seek immediate medical attention if these symptoms occur [see Warnings and Precautions (5.2)].

Depression and Suicide

Advise patients that depression and suicidal ideation have been reported during the use of BETASERON. Inform patients of the symptoms of depression or suicidal ideation, and instruct patients to report them immediately to their healthcare provider [see Warnings and Precautions (5.3)].

Congestive Heart Failure

Advise patients that worsening of pre-existing congestive heart failure have been reported in patients using BETASERON.

Advise patients of symptoms of worsening cardiac condition, and instruct patients to report them immediately to their healthcare provider [see Warnings and Precautions (5.4)].

Injection Site Reactions Including Necrosis

Advise patients that injection site reactions occur in most patients treated with BETASERON, and that injection site necrosis may occur at one or multiple sites. Instruct patients to promptly report any break in the skin, which may be associated with blue-black discoloration, swelling, or drainage of fluid from the injection site, prior to continuing their BETASERON therapy [see Warnings and Precautions (5.5)].

Pulmonary Arterial Hypertension

Inform patients that PAH has occurred in patients treated with interferon beta products, including BETASERON. Instruct patients to promptly report any new symptoms such as new or increasing fatigue or shortness of breath to their healthcare provider [see Warnings and Precautions (5.8)].

Flu-like Symptom Complex

Inform patients that flu-like symptoms are common following initiation of therapy with BETASERON, and that concurrent use of analgesics and/or antipyretics on treatment days may help ameliorate flu-like symptoms associated with BETASERON use [see Warnings and Precautions (5.9) and Dosage and Administration (2.4)].

Seizures

Instruct patients to report seizures immediately to their healthcare provider [see Warnings and Precautions (5.10)].

Pregnancy

Advise patients to notify their healthcare provider if they are pregnant or plan to become pregnant [see Use in Specific Populations (8.1)].

Medication Guide

BETASERON
(bay-ta-seer-on)

interferon beta-1b
(in-ter-feer-on beta-one-be)

What is the most important information I should know about BETASERON?

BETASERON can cause serious side effects, including:

- liver problems including liver failure. Symptoms of liver problems may include:

- yellowing of your eyes

- itchy skin

- nausea or vomiting

- feeling very tired

- flu-like symptoms

- bruising easily or bleeding problems

Your healthcare provider will do blood tests to check for these problems while you take BETASERON.

- serious allergic reactions. Serious allergic reactions can happen quickly and may happen after your first dose of BETASERON or after you have taken BETASERON many times. Symptoms may include difficulty breathing or swallowing, swelling of the mouth or tongue, rash, itching, or skin bumps.
- depression or suicidal thoughts. Call your healthcare provider right away if you have any of the following symptoms, especially if they are new, worse, or worry you:

- thoughts about suicide or dying

- new or worse depression

- new or worse anxiety

- trouble sleeping (insomnia)

- acting aggressive, being angry, or violent

- acting on dangerous impulses

- hallucinations

- other unusual changes in behavior or mood

What is BETASERON?

BETASERON is a prescription medicine used to treat relapsing forms of multiple sclerosis, to include clinically isolated syndrome, relapsing-remitting disease, and active secondary progressive disease, in adults. BETASERON is similar to certain interferon proteins that are produced in the body.

It is not known if BETASERON is safe and effective in children.

Who should not take BETASERON?

Do not take BETASERON if you are allergic to interferon beta-1b, to another interferon beta, to human albumin, or mannitol. See the end of this leaflet for a complete list of ingredients in BETASERON.

What should I tell my healthcare provider before taking BETASERON?

Before you take BETASERON, tell your healthcare provider if you:

- have or have had depression (sinking feeling or sadness), anxiety (feeling uneasy, nervous, or fearful for no reason) or trouble sleeping
- have or have had liver problems
- have or have had blood problems such as bleeding or bruising easily, low red blood cells (anemia) or low white blood cells
- have or have had seizures
- have or have had heart problems
- are pregnant or plan to become pregnant.
- are breastfeeding or plan to breastfeed. It is not known if BETASERON passes into your breast milk.

Tell your healthcare provider about all the medicines you take, including prescription and nonprescription medicines, vitamins, and herbal supplements.

Know the medicines you take. Keep a list of them to show your healthcare provider and pharmacist when you get a new medicine.

How should I take BETASERON?

- See the Instructions for Use at the end of this Medication Guide for complete information on how to use BETASERON.
- BETASERON is given by injection under your skin (subcutaneous injection) every other day.
- Take BETASERON exactly as your healthcare provider tells you to take it.
- If your healthcare provider feels that you or someone else may give you the injections then you or the other person should be trained by your healthcare provider in how to give an injection.
- Do not try to give yourself or have another person give you injections until you or both of you understand and are comfortable with how to prepare your dose and give the injection.
- You may be started on a lower dose when you first start taking BETASERON. Your healthcare provider will tell you what dose of BETASERON to use.
- Your healthcare provider may change your dose of BETASERON. You should not change your dose without talking to your healthcare provider.
- If you miss a dose, you should take your next dose as soon as you remember or are able to take it. Your next injection should be taken about 48 hours (2 days) after that dose. Do not take BETASERON on 2 consecutive days. If you accidentally take more than your prescribed dose, or take it on 2 consecutive days, call your healthcare provider right away.
- Always use a new, unopened vial of BETASERON and pre-filled diluent syringe for each injection. Throw away any unused medicine. Do not re-use any vials, syringes, or needles.
- It is important for you to change your injection site each time you inject BETASERON. This will lessen the chance of you having a serious skin reaction at the site where you inject BETASERON. Avoid injecting BETASERON into an area of skin that is sore, reddened, infected or has other problems.

What are the possible side effects of BETASERON?

BETASERON may cause serious side effects. Call your healthcare provider right away if you have any of the serious side effects of BETASERON including:

- See "What is the most important information I should know about BETASERON?"
- heart problems. BETASERON may worsen heart problems including congestive heart failure. Symptoms of heart problems may include:

- swollen ankles

- shortness of breath

- not being able to lay flat in bed

- tightness in chest

- decreased ability to exercise

- fast heartbeat

- increased need to urinate at night

- injection site problems. Serious skin reactions can happen in some people including areas of severe damage to skin and the tissue below the skin (necrosis). These reactions can happen anywhere you inject BETASERON. Symptoms of injection site problems may include swelling, redness, or pain at the injection site, fluid drainage from the injection site, and breaks in your skin or blue-black skin discoloration. Call your healthcare provider right away if an injection site becomes swollen and painful or the area looks infected. You may have a skin infection or an area of severe skin damage (necrosis) requiring treatment by a healthcare provider.
- Pulmonary arterial hypertension. Pulmonary arterial hypertension can occur with interferon beta products, including BETASERON. Symptoms may include new or increasing fatigue or shortness of breath. Contact your healthcare provider right away if you develop these symptoms.
- flu-like symptoms. BETASERON can cause flu-like symptoms including:

- fever

- tiredness

- sweating

- chills

- muscle aches when you first start to use it

These symptoms may decrease over time. Taking medicines for fever and pain relief on the days you are using BETASERON may help decrease these symptoms.

- seizures. Some people have had seizures while taking BETASERON, including people who have never had seizures before. It is not known if the seizures were related to their MS, to BETASERON, or to a combination of both. If you have a seizure after taking BETASERON call your healthcare provider right away.

The most common side effects of BETASERON include:

- low white blood cell count

- increases in your liver enzymes

- problems sleeping

- headache

- increases in your muscle tension

- weakness

- pain

- rash

- stomach pain

Tell your healthcare provider if you have any side effect that bothers you or that does not go away.

These are not all the possible side effects of BETASERON. For more information, ask your healthcare provider or pharmacist.

Call your doctor for medical advice about side effects. You may report side effects to FDA at 1-800-FDA-1088.

How should I store BETASERON?

- Before mixing, store BETASERON between 36°F to 86°F (2°C to 30°C).
- After mixing, you can refrigerate BETASERON for up to 3 hours before using. Your BETASERON must be used within 3 hours of mixing even if refrigerated.
- Do not freeze.

Keep BETASERON and all medicines out of the reach of children.

General information about the safe and effective use of BETASERON.

Medicines are sometimes prescribed for purposes other than those listed in a Medication Guide. Do not use BETASERON for a condition for which it was not prescribed. Do not give BETASERON to other people, even if they have the same symptoms that you have. It may harm them.

This Medication Guide summarizes the most important information about BETASERON. If you would like more information, talk with your healthcare provider. You can ask your pharmacist or healthcare provider for information about BETASERON that is written for health professionals.

For more information, go to www.BETASERON.com or call BETAPLUS, the BETASERON patient support program, at 1-800-788-1467.

What are the ingredients in BETASERON?

Active ingredient: interferon beta-1b

Inactive ingredients: albumin (human), mannitol

Diluent contains sodium chloride solution.

This Medication Guide has been approved by the U.S. Food and Drug Administration Revised: 7/2023

Instructions for Use

BETASERON
(bay-ta-seer-on)

interferon beta-1b
(in-ter-feer-on beta-one-be)

Read the Instructions for Use that come with your BETASERON before you start using it and each time you get a refill. There may be new information. This leaflet does not take the place of talking to your healthcare provider about your medical condition or treatment. Before you use BETASERON for the first time, make sure your healthcare provider shows you the right way to use it.

Supplies needed for your BETASERON Injection (See Figure A).

- 1 single-dose carton containing:
- A vial of BETASERON
- A pre-filled diluent syringe
- A vial adapter with a 30-gauge needle attached (in the blister pack)
- 2 alcohol prep pads

Step 1: Preparing for Your BETASERON Injection

- Place the supplies you will need on a clean, flat surface in a well-lit area.
- Check the expiration date on the single-dose carton to make sure that it has not expired. Do not use it if the medication has expired.
- Wash your hands thoroughly with soap and water.
- Open the single-dose carton and take out all the contents. Make sure the blister pack containing the vial adapter is sealed. Check to make sure the plastic cap on the pre-filled diluent syringe is firmly attached.
- Remove the tray from the single-dose carton and place it on a flat surface.
- Place the BETASERON vial in the well (vial holder) and place the pre-filled diluent syringe in the U-shaped trough (See Figure B).

Step 2: Mixing BETASERON

- Remove the BETASERON vial from the well (vial holder) and take the cap off the vial.
- Place the vial back into the well (vial holder).
- Use an alcohol prep pad to clean the top of the vial. Move the alcohol prep pad in 1 direction. Leave the alcohol prep pad on top of the vial.
- Peel the label off the blister pack with the vial adapter in it. The vial adapter is sterile. Do not remove or touch the vial adapter.
- Remove the alcohol prep pad from the top of the BETASERON vial. Pick up the vial adapter in the blister pack. Turn over the blister pack keeping the vial adapter inside. Put the adapter on top of the BETASERON vial. Push down on the adapter until it pierces the rubber top of the BETASERON vial and snaps in place (See Figure C). Remove the blister packaging from the vial adapter.

- Twist the plastic cap from the pre-filled diluent syringe. Throw away the plastic cap (See Figure D).

- Keep the vial adapter attached to the vial and remove the vial from the well (vial holder). Be careful not to pull the vial adapter off the top of the vial.
- Connect the pre-filled diluent syringe to the vial adapter by turning clockwise until resistance is felt and the attachment is secure. This forms the syringe assembly (See Figure E).

- Slowly push the plunger of the pre-filled diluent syringe all the way in. This will transfer all of the liquid from the syringe into the BETASERON vial (See Figure F). The plunger may return to its original position after you release it.

- Gently swirl the vial to completely dissolve the white powder of BETASERON. Do not shake. Shaking and even gentle mixing can cause foaming of the medicine. If there is foam, let the vial sit until the foam settles before using it.
- After the powder dissolves, look closely at the solution in the vial. Do not use the solution if it is cloudy or contains particles. It should be clear and colorless.
- Do not use cracked or damaged BETASERON vials. If your vial is cracked or damaged, get a new single-dose carton containing a BETASERON vial, pre-filled diluent syringe, vial adapter and 2 alcohol prep pads. Repeat the steps to prepare your BETASERON dose.
- Contact BETAPLUS, the BETASERON patient support program, at 1-800-788-1467 to obtain a replacement product.

Step 3: Preparing the Injection

You have completed the steps to prepare your BETASERON and are ready for the injection. The injection should be given immediately after mixing and allowing any foam in the solution to settle. If you must wait to give yourself the injection, you may refrigerate the solution and use within 3 hours of mixing your BETASERON. Do not freeze.

- Push the plunger in and hold it there; then turn the syringe assembly so that the syringe is horizontal and the vial is on top.
- Slowly pull the plunger back to withdraw all the liquid from the BETASERON vial into the syringe (See Figure G).
- NOTE: The syringe barrel is marked with numbers from 0.25 mL to 1 mL (See Figure H). If the solution in the vial cannot be drawn up to the 1 mL mark, discard the vial and syringe and start over with a new single-dose carton containing a BETASERON vial, pre-filled diluent syringe, vial adapter and alcohol prep pads.
- Turn the syringe assembly so that the needle end is pointing up. Remove any air bubbles by tapping the outside of the syringe with your fingers. Slowly push the plunger to the 1 mL mark on the syringe or to the mark that matches the amount of BETASERON prescribed by your healthcare provider (See Figure H). If too much solution is pushed into the vial, repeat Step 3.

- Turn the syringe assembly so that the vial is at the bottom. Remove the vial adapter and the vial from the syringe by twisting the vial adapter. This will remove the vial adapter and the vial from the syringe, but will leave the needle on the syringe (See Figure I).

Step 4: Choosing an Injection Site

- BETASERON (interferon beta-1b) is injected under the skin and into the fat layer between the skin and the muscles (subcutaneous tissue). The best areas for injection are where the skin is loose and soft and away from the joints, nerves, and bones. Do not use the area near your navel or waistline. If you are very thin, use only the thigh or outer surface of the arm for injection.
- Choose a different site each time you give yourself an injection. Figure J shows different areas for giving injections. Do not inject in the same area for 2 injections in a row. Keep a record of your injections to help make sure you change (rotate) your injection sites. You should decide where you will inject BETASERON before you prepare your medicine for injection. If there are any sites that are difficult for you to reach, you can ask someone who has been trained to give the injection to help you.

- Do not inject BETASERON in a site where the skin is red, bruised, infected, or scabbed, has broken open, or has lumps, bumps, or pain. Tell your healthcare provider if you find skin conditions like the ones mentioned here or any other unusual-looking areas where you have been given injections.

Step 5: Injecting BETASERON

- Using a circular motion, clean the injection site with an alcohol prep pad, starting at the injection site and moving outward. Let the skin area air dry.
- Remove the cap from the needle. Hold the syringe like a pencil or dart in 1 hand.
- Gently pinch the skin around the site with the thumb and forefinger of the other hand (See Figure K). Insert the needle straight up and down into your skin at a 90° angle with a quick, dart-like motion.

- Slowly push the plunger all the way in until the syringe is empty (See Figure L).

- Remove the needle from the skin. Place a dry cotton ball or gauze pad over the injection site. Gently massage the injection site for a few moments with the dry cotton ball or gauze pad. Throw away the syringe in your puncture-proof disposal container.
- Optional Use of BETACONNECT Autoinjector:
  You may also give BETASERON by using the BETACONNECT autoinjector. You should get help with training on the use of the BETACONNECT autoinjector from a healthcare provider before using it for the first time. The BETACONNECT autoinjector should only be used with the syringes that come in the BETASERON packaging. See the Instructions for Use that come with the BETACONNECT autoinjector. For more information, call BETAPLUS, the BETASERON patient support program, at 1-800-788-1467.

Step 6: Disposing of used syringes, needles, and vials

- To prevent needle-stick injury and spread of infection, do not try to re-cap the needle.
- Place used needles, syringes, and vials in a closeable, puncture-resistant container. You may use a sharps container (such as a red biohazard container), hard plastic container (such as a detergent bottle), or metal container (such as an empty coffee can). Do not use glass or clear plastic containers. Ask your healthcare provider for instructions on the right way to throw away (dispose of) the container. There may be state and local laws about how you should throw away used needles and syringes.
- Do not throw used needles, syringes, or vials in your household trash or recycle.
- Throw away any unused medicine. Do not save any unused BETASERON for a future dose.
- Keep the disposal container, needles, syringes, and vials of BETASERON out of the reach of children.

This Instructions for Use has been approved by the U.S. Food and Drug Administration 11/2021

Manufactured for:

Bayer HealthCare Pharmaceuticals Inc.
Whippany, NJ 07981

Manufactured in Austria

U.S. License No. 1778

© 1993 Bayer HealthCare Pharmaceuticals Inc. All rights reserved.

PACKAGE LABEL

The principal display panel is a representative example and may not reflect the most current label.
NDC 50419-524-01 Rx only

BETASERON
(interferon beta-1b)

For injection

0.3 mg per vial

For subcutaneous injection

No U.S. standard of potency

Single use carton

Contains:

- 1 single-use vial for reconstitution
- 1 pre-filled single-use sodium chloride 0.54% solution diluent syringe
- 1 vial adapter with a 30 gauge needle attached
- 2 alcohol prep pads